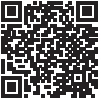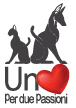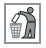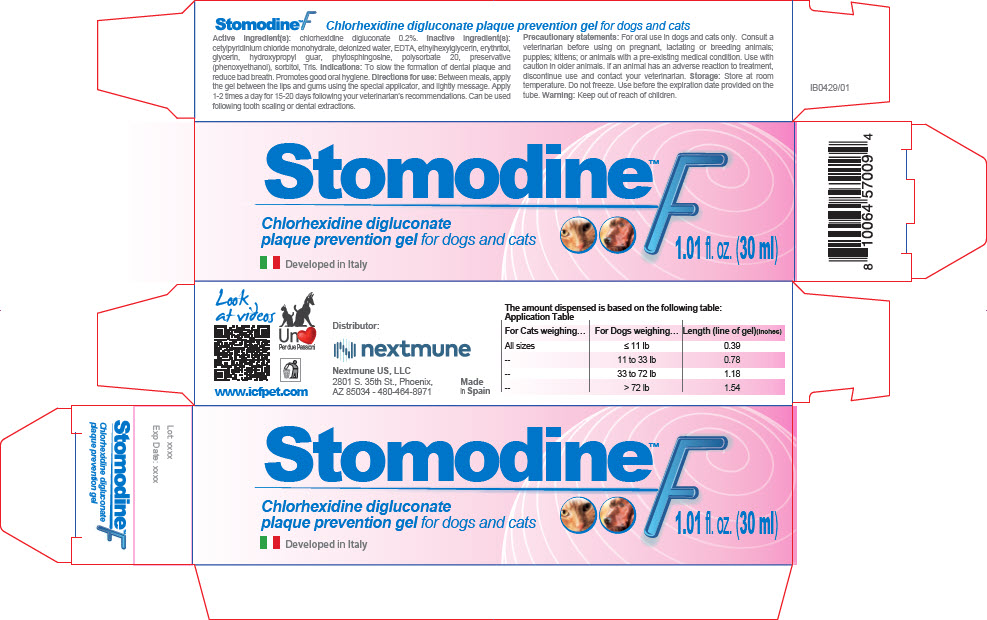 DRUG LABEL: Stomodine F
NDC: 86127-010 | Form: GEL
Manufacturer: Nextmune AB
Category: animal | Type: OTC ANIMAL DRUG LABEL
Date: 20220112

ACTIVE INGREDIENTS: CHLORHEXIDINE GLUCONATE 2 mg/1 mL
INACTIVE INGREDIENTS: CETYLPYRIDINIUM CHLORIDE; WATER; EDETIC ACID; ETHYLHEXYLGLYCERIN; ERYTHRITOL; GLYCERIN; PHYTOSPHINGOSINE; POLYSORBATE 20; PHENOXYETHANOL; SORBITOL; TROMETHAMINE; GUARAPROLOSE (3500 MPA.S AT 1%)

Stomodine™ F

Stomodine™F Chlorhexidine digluconate plaque prevention gel for dogs and cats

Active ingredient(s): chlorhexidine digluconate 0.2%.

Inactive ingredient(s): cetylpyridinium chloride monohydrate, deionized water, EDTA, ethylhexylglycerin, erythritol, glycerin, hydroxypropyl guar, phytosphingosine, polysorbate 20, preservative (phenoxyethanol), sorbitol, Tris.

VETERINARY INDICATIONS

Indications: To slow the formation of dental plaque and reduce bad breath. Promotes good oral hygiene.

DOSAGE AND ADMINISTRATION

Directions for use: Between meals, apply the gel between the lips and gums using the special applicator, and lightly message. Apply 1-2 times a day for 15-20 days following your veterinarian's recommendations. Can be used following tooth scaling or dental extractions.

PRECAUTIONS

Precautionary statements: For oral use in dogs and cats only. Consult a veterinarian before using on pregnant, lactating or breeding animals; puppies; kittens; or animals with a pre-existing medical condition. Use with caution in older animals. If an animal has an adverse reaction to treatment, discontinue use and contact your veterinarian.

STORAGE AND HANDLING

Storage: Store at room temperature. Do not freeze. Use before the expiration date provided on the tube.

Warning: Keep out of reach of children.

Look
at videos

www.icfpet.com

Distributor:
Nextmune US, LLC
2801 S. 35th St., Phoenix,
AZ 85034 - 480-464-8971

Made
in Spain

The amount dispensed is based on the following table:

Application Table
For Cats weighing… | For Dogs weighing… | Length (line of gel)(inches)
All sizes | ≤ 11 lb | 0.39
-- | 11 to 33 lb | 0.78
-- | 33 to 72 lb | 1.18
-- | > 72 lb | 1.54

PRINCIPAL DISPLAY PANEL - 30 ml Tube Carton

Stomodine™ F
Chlorhexidine digluconate
plaque prevention gel for dogs and cats

Developed in Italy

1.01 fl. oz. (30 ml)